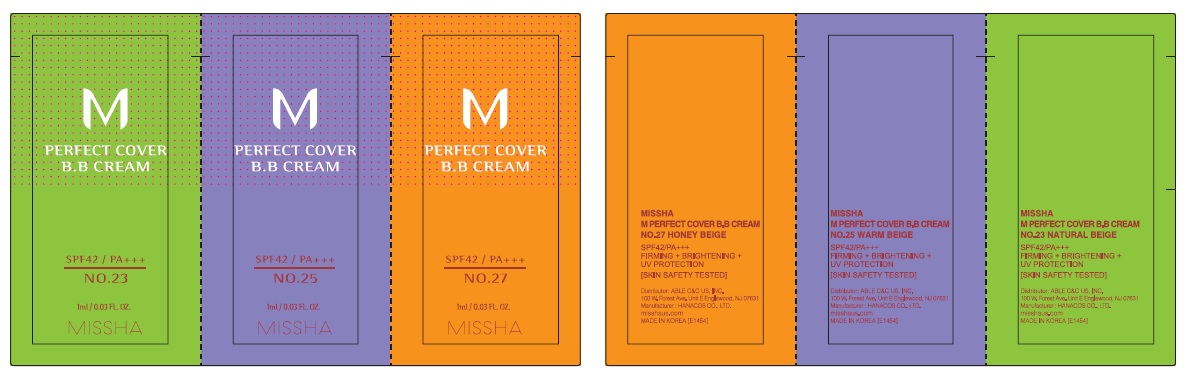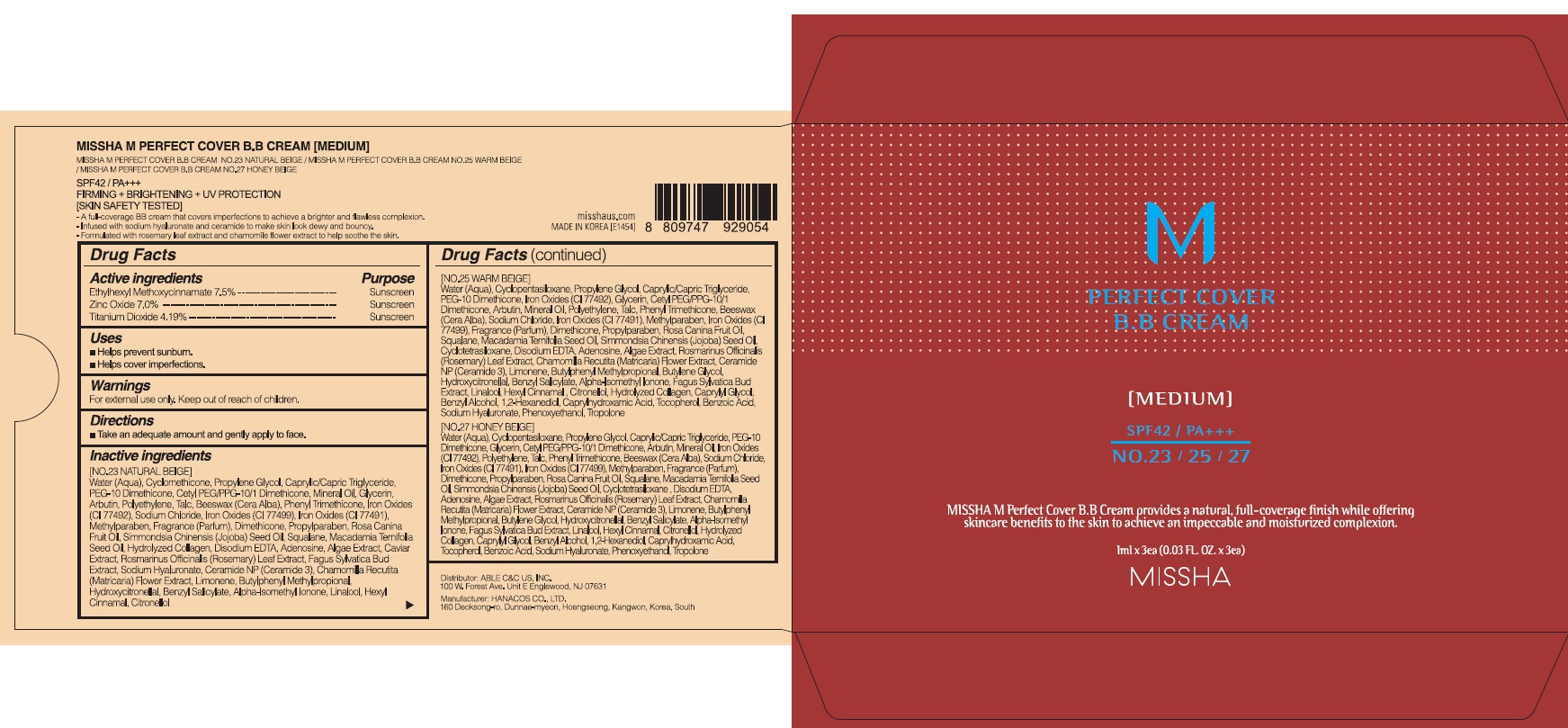 DRUG LABEL: MISSHA M PERFECT COVER BB
NDC: 13733-453 | Form: KIT | Route: TOPICAL
Manufacturer: ABLE C&C CO., LTD.
Category: otc | Type: HUMAN OTC DRUG LABEL
Date: 20210426

ACTIVE INGREDIENTS: OCTINOXATE 7.5 g/100 mL; Zinc Oxide 7.0 g/100 mL; Titanium Dioxide 4.19 g/100 mL; OCTINOXATE 7.5 g/100 mL; Zinc Oxide 7.0 g/100 mL; Titanium Dioxide 4.19 g/100 mL; OCTINOXATE 7.5 g/100 mL; Zinc Oxide 7.0 g/100 mL; Titanium Dioxide 4.19 g/100 mL
INACTIVE INGREDIENTS: WATER; Cyclomethicone; WATER; CYCLOMETHICONE 5; WATER; CYCLOMETHICONE 5

ACTIVE INGREDIENTS

Ethylhexyl Methoxycinnamate 7.5%
Zinc Oxide 7.0%
Titanium Dioxide 4.19%

INACTIVE INGREDIENTS

[NO.23 NATURAL BEIGE]
Water (Aqua), Cyclomethicone, Propylene Glycol, Caprylic/Capric Triglyceride, PEG-10 Dimethicone, Cetyl PEG/PPG-10/1 Dimethicone, Mineral Oil, Glycerin, Arbutin, Polyethylene, Talc, Beeswax (Cera Alba), Phenyl Trimethicone, Iron Oxides (CI 77492), Sodium Chloride, Iron Oxides (CI 77499), Iron Oxides (CI 77491), Methylparaben, Fragrance (Parfum), Dimethicone, Propylparaben, Rosa Canina Fruit Oil, Simmondsia Chinensis (Jojoba) Seed Oil, Squalane, Macadamia Ternifolia Seed Oil, Hydrolyzed Collagen, Disodium EDTA, Adenosine, Algae Extract, Caviar Extract, Rosmarinus Officinalis (Rosemary) Leaf Extract, Fagus Sylvatica Bud Extract, Sodium Hyaluronate, Ceramide NP (Ceramide 3), Chamomilla Recutita (Matricaria) Flower Extract, Limonene, Butylphenyl Methylpropional, Hydroxycitronellal, Benzyl Salicylate, Alpha-Isomethyl Ionone, Linalool, Hexyl Cinnamal, Citronellol

[NO.25 WARM BEIGE]
Water (Aqua), Cyclopentasiloxane, Propylene Glycol, Caprylic/Capric Triglyceride, PEG-10 Dimethicone, Iron Oxides (CI 77492), Glycerin, Cetyl PEG/PPG-10/1 Dimethicone, Arbutin, Mineral Oil, Polyethylene, Talc, Phenyl Trimethicone, Beeswax (Cera Alba), Sodium Chloride, Iron Oxides (CI 77491), Methylparaben, Iron Oxides (CI 77499), Fragrance (Parfum), Dimethicone, Propylparaben, Rosa Canina Fruit Oil, Squalane, Macadamia Ternifolia Seed Oil, Simmondsia Chinensis (Jojoba) Seed Oil, Cyclotetrasiloxane, Disodium EDTA, Adenosine, Algae Extract, Rosmarinus Officinalis (Rosemary) Leaf Extract, Chamomilla Recutita (Matricaria) Flower Extract, Ceramide NP (Ceramide 3), Limonene, Butylphenyl Methylpropional, Butylene Glycol, Hydroxycitronellal, Benzyl Salicylate, Alpha-Isomethyl Ionone, Fagus Sylvatica Bud Extract, Linalool, Hexyl Cinnamal , Citronellol, Hydrolyzed Collagen, Caprylyl Glycol, Benzyl Alcohol, 1,2-Hexanediol, Caprylhydroxamic Acid, Tocopherol, Benzoic Acid, Sodium Hyaluronate, Phenoxyethanol, Tropolone

[NO.27 HONEY BEIGE]
Water (Aqua), Cyclopentasiloxane, Propylene Glycol, Caprylic/Capric Triglyceride, PEG-10 Dimethicone, Glycerin, Cetyl PEG/PPG-10/1 Dimethicone, Arbutin, Mineral Oil, Iron Oxides (CI 77492), Polyethylene, Talc, Phenyl Trimethicone, Beeswax (Cera Alba), Sodium Chloride, Iron Oxides (CI 77491), Iron Oxides (CI 77499), Methylparaben, Fragrance (Parfum), Dimethicone, Propylparaben, Rosa Canina Fruit Oil, Squalane, Macadamia Ternifolia Seed Oil, Simmondsia Chinensis (Jojoba) Seed Oil, Cyclotetrasiloxane , Disodium EDTA, Adenosine, Algae Extract, Rosmarinus Officinalis (Rosemary) Leaf Extract, Chamomilla Recutita (Matricaria) Flower Extract, Ceramide NP (Ceramide 3), Limonene, Butylphenyl Methylpropional, Butylene Glycol, Hydroxycitronellal, Benzyl Salicylate, Alpha-Isomethyl Ionone, Fagus Sylvatica Bud Extract, Linalool, Hexyl Cinnamal, Citronellol, Hydrolyzed Collagen, Caprylyl Glycol, Benzyl Alcohol, 1,2-Hexanediol, Caprylhydroxamic Acid, Tocopherol, Benzoic Acid, Sodium Hyaluronate, Phenoxyethanol, Tropolone

PURPOSE

Sunscreen

WARNINGS

For external use only. Keep out of reach of children. Stop use and ask doctor if irritation or rash occurs. Do not use on broken or damaged skin. Do not store in direct sunlight.

KEEP OUT OF REACH OF CHILDREN

Uses

■ Helps prevent sunburn.
■ Helps cover imperfections.

Directions

■ Take an adequate amount and gently apply to face.